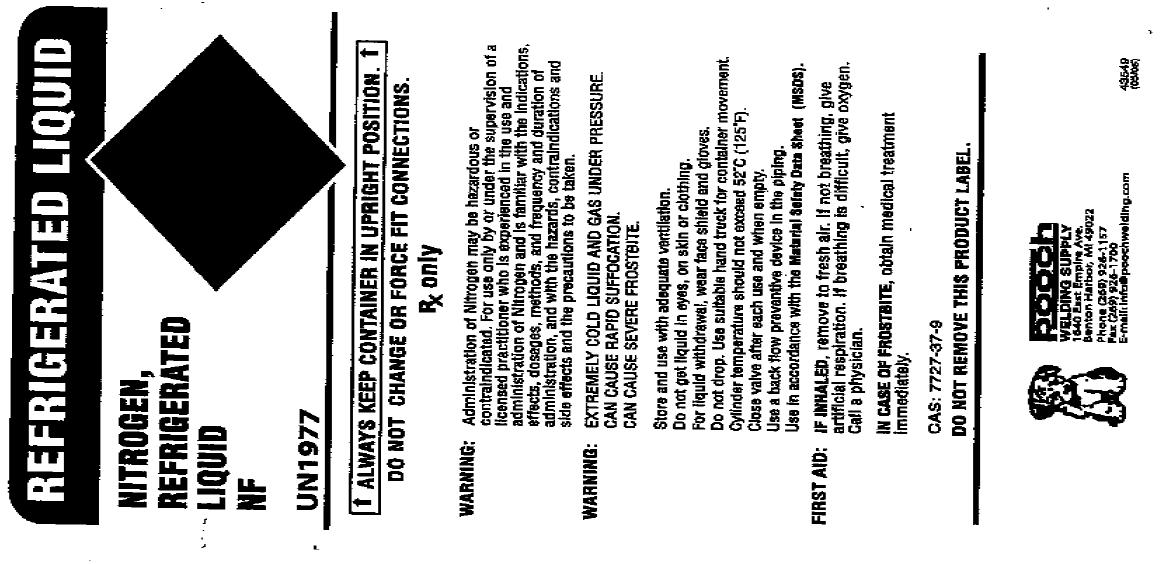 DRUG LABEL: Nitrogen
NDC: 51613-002 | Form: GAS
Manufacturer: Pooch Welding Supply Company, Inc.
Category: prescription | Type: HUMAN PRESCRIPTION DRUG LABEL
Date: 20100618

ACTIVE INGREDIENTS: Nitrogen 990 mL/1 L

nitrogen

PACKAGE LABEL

REFRIGERATED LIQUID
NITROGEN, REFRIGERATED LIQUID NF UN1977
NON-FLAMMABLE GAS 2 ALWAYS KEEP CONTAINER IN UPRIGHT POSITION DO NOT CHANGE OR FORCE FIT CONNECTIONS.
Rx only. WARNING: Administration of Nitrogen may be hazardous or contraindicated. For use only by or under supervision of a licensed practitioner who is experienced in the use and administration of Nitrogen and is familiar with the indications, effects, dosages, methods, and frequency and duration of administration, and with the hazards, contraindications, and side effects and the precautions to be taken.
WARNING: EXTREMELY COLD LIQUID AND GAS UNDER PRESSURE. CAN CAUSE RAPID SUFFOCATION. CAN CAUSE SEVERE FROSTBITE. Store and use with adequate ventilation. Do not get liquid in eyes, on skin, or clothing. For liquid withdrawal, wear face shield and gloves. Do not drop. Use suitable hand truck for container movement. Cylinder temperatures should not exceed 52C (125F). Close valve after each use and when empty. Use a back flow preventive device in the piping. Use in accordance with the Material Safety Data Sheet (MSDS).
FIRST AID: IF INHALED, remove to fresh air. If not breathing, give oxygen. If breathing is difficult, give oxygen. Call a physician. IN CASE OF FROSTBITE, obtain medical treatment immediately. CAS: 7727-37-9 DO NOT REMOVE THIS PRODUCT LABEL.
POOCH WELDING SUPPLY 1540 East Empire Ave. Benton Harbor, MI 49022 Phone (269) 926-1157 Fax (269) 926-1700 E-mail: info@poochwelding.com
43549 (05/05)